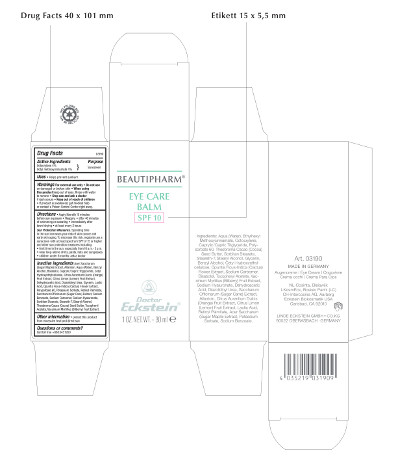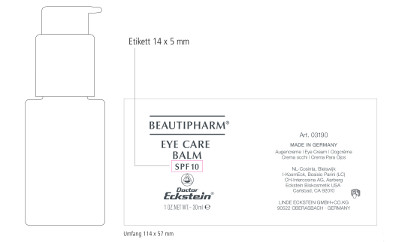 DRUG LABEL: Beautipharm Eye Care Balm
NDC: 6889-0319 | Form: CREAM
Manufacturer: Linde Eckstein GmbH + Co. KG
Category: otc | Type: HUMAN OTC DRUG LABEL
Date: 20161005

ACTIVE INGREDIENTS: OCTOCRYLENE 1.33 g/30 mL; OCTINOXATE 1.33 g/30 mL
INACTIVE INGREDIENTS: WATER 9.335 g/30 mL; MEDIUM-CHAIN TRIGLYCERIDES 3.33 g/30 mL; POLYSORBATE 60 3.33 g/30 mL; COCOA BUTTER 3.33 g/30 mL; SORBITAN MONOSTEARATE 3.33 g/30 mL; STEARETH-7 1 g/30 mL; STEARYL ALCOHOL 1 g/30 mL; GLYCERIN 1 g/30 mL; BENZYL ALCOHOL 0.3 g/30 mL; CETYL HYDROXYETHYLCELLULOSE (350000 MW) 0.3 g/30 mL; OPUNTIA FICUS-INDICA FLOWER 0.3 g/30 mL; CARBOMER HOMOPOLYMER TYPE C 0.16 g/30 mL; LEVOMENOL 0.1 g/30 mL; .ALPHA.-TOCOPHEROL ACETATE, DL- 0.1 g/30 mL; BILBERRY 0.1 g/30 mL; HYALURONATE SODIUM 0.1 g/30 mL; DEHYDROACETIC ACID 0.09 g/30 mL; DIAZOLIDINYL UREA 0.03 g/30 mL; SUGARCANE 0.03 g/30 mL; ALLANTOIN 0.03 g/30 mL; ORANGE 0.01 g/30 mL; LEMON 0.01 g/30 mL; LACTIC ACID 0.01 g/30 mL; VITAMIN A PALMITATE 0.01 g/30 mL; ACER SACCHARUM BARK/SAP 0.003 g/30 mL; POTASSIUM SORBATE 0.001 g/30 mL; SODIUM BENZOATE 0.001 g/30 mL

Beautipharm® Eye Care Balm

Beautipharm® Eye Care Balm

SPF 10

1 OZ. NET.WT. – 30 ml

Art. 03190

MADE IN GERMANY

Augencreme - Eye Cream – Oogcrème – Crema occhi – Crema Para Ojos

Ingredients: Aqua (Water), Ethylhexyl Methoxycinnamate, Octocrylene, Caprylic/Capric Triglyceride, Polysorbate 60, Theobroma Cacao (Cocoa) Seed Butter, Sorbitan Stearate, Steareth-7, Stearyl Alcohol, Glycerin, Benzyl Alcohol, Cetyl Hydroxyethylcellulose, Opuntia Ficus-Indica (Cactus) Flower Extract, Sodium Carbomer, Bisabolol, Tocopheryl Acetate, Vaccinium Myrtillus (Bilberry) Fruit Extract, Sodium Hyaluronate, Dehydroacetic Acid, Diazolidinyl Urea, Saccharum Officinarum (Sugar Cane) Extract, Allantoin, Citrus Aurantium Dulcis (Orange) Fruit Extract, Citrus Limon (Lemon) Fruit Extract, Lactic Acid, Retinyl Palmitate, Acer Saccharum (Sugar Maple) Extract, Potassium Sorbate, Sodium Benzoate.

NL-Cosinta, Bleiswijk

KosmEck Italia – Bosisio Parini (LC)

CH-Intercosina AG, Aarberg

Eckstein Biokosmetik USA

Carlsbad, CA 92010

LINDE ECKSTEIN GMBH+CO.KG

90522 OBERASBACH · GERMANY

Drug Facts

Active Ingredients

Octocrylene 4%

Octyl methoxycinnamate 4%

Purpose

Sunscreen

Uses

• Helps prevent sunburn

Warnings For external use only

• Do not use on damaged or broken skin

• When using this product keep out of eyes. Rinse with water to remove

• Stop use and ask a doctor if rash occurs

• Keep out of reach of children

• If product is swallowed, get medical help or contact a Poison Control Center right away.

Directions

• Apply liberally 15 minutes before sun exposure

• Reapply:

• after 40 minutes of swimming or sweating

• immediately after towel drying

• at least every 2 hours

Sun Protection Measures.

Spending time in the sun increases your risk of skin cancer and early skin aging. To decrease this risk, regularly use a sunscreen with a broad spectrum SPF of 15 or higher and other sun protection measures including:

• limit time in the sun, especially from 10 a.m. - 2 p.m.

• wear long-sleeve shirts, pants, hats and sunglasses

• children under 6 months: ask a doctor

Inactive ingredients

Acer Saccharum (Sugar Maple) Extract, Allantoin, Aqua (Water), Benzyl Alcohol, Bisabolol, Caprylic/Capric Triglyceride, Cetyl Hydroxyethylcellulose, Citrus Aurantium Dulcis (Orange) Fruit Extract, Citrus Limon (Lemon) Fruit Extract, Dehydroacetic Acid, Diazolidinyl Urea, Glycerin, Lactic Acid, Opuntia Ficus-Indica (Cactus) Flower Extract, Polysorbate 60, Potassium Sorbate, Retinyl Palmitate, Saccharum Officinarum (Sugar Cane) Extract, Sodium Benzoate, Sodium Carbomer, Sodium Hyaluronate, Sorbitan Stearate, Steareth-7, Stearyl Alcohol, Theobroma Cacao (Cocoa) Seed Butter, Tocopheryl Acetate, Vaccinium Myrtillus (Bilberry) Fruit Extract.

Other information

• protect this product from excessive heat and direct sun

Questions or comments?

Call toll free +888 345 1950

Beautipharm® Eye Care Balm

SPF10

1 OZ.NET.WT.– 30 ml

Art. 03190

MADE IN GERMANY

Augencreme - Eye Cream – Oogcrème – Crema occhi – Crema Para Ojos

NL-Cosinta, Bleiswijk

KosmEck Italia – Bosisio Parini (LC)

CH-Intercosina AG, Aarberg

Eckstein Biokosmetik USA

Carlsbad, CA 92010

LINDE ECKSTEIN GMBH+CO.KG

90522 OBERASBACH · GERMANY